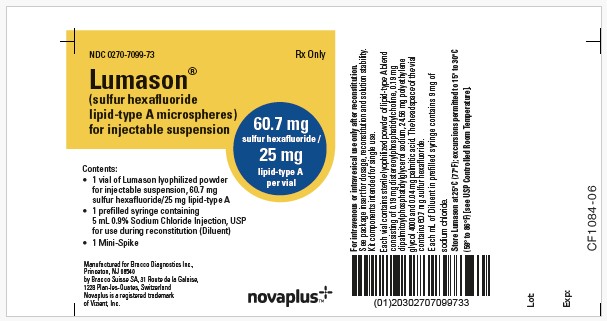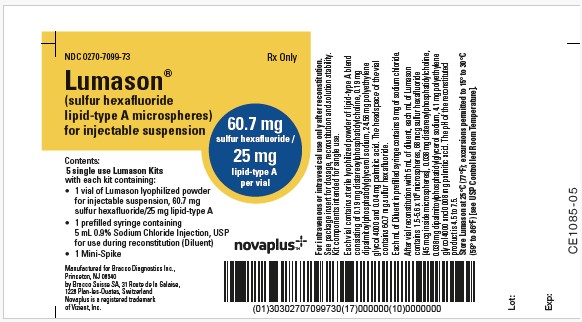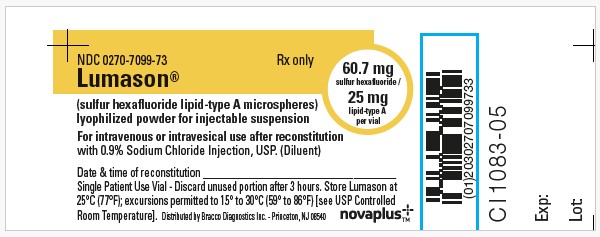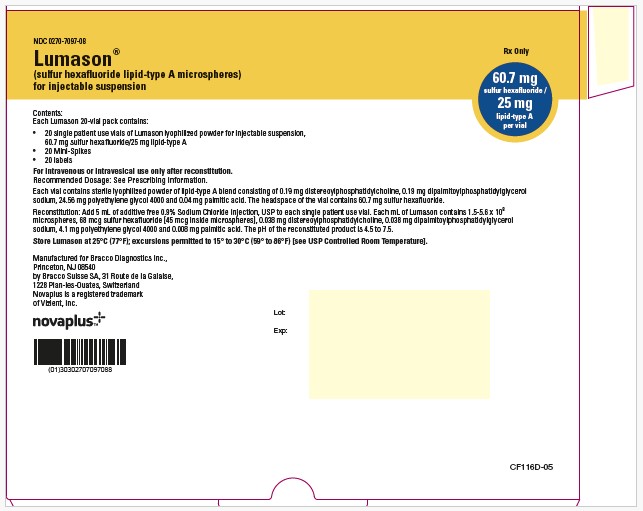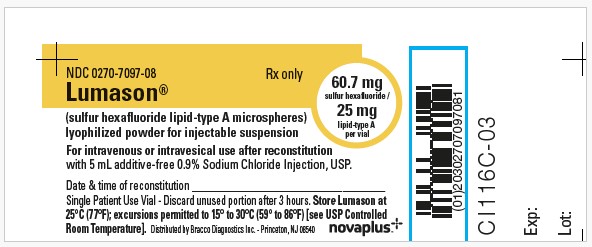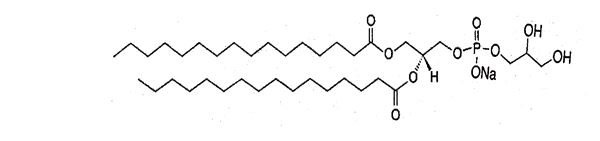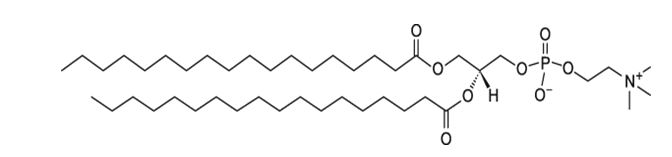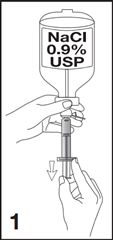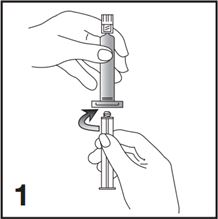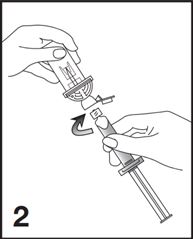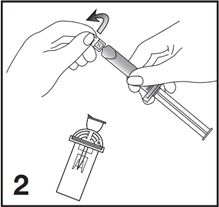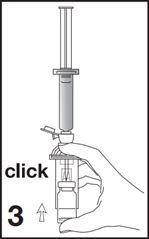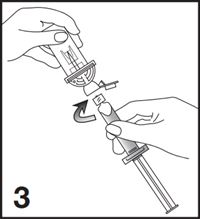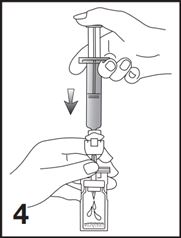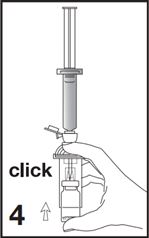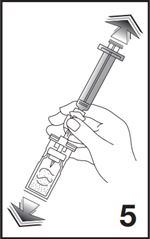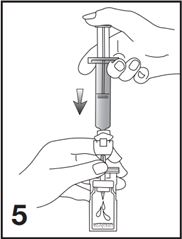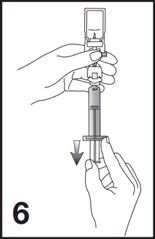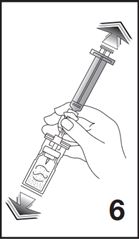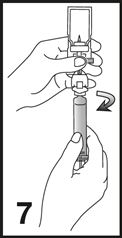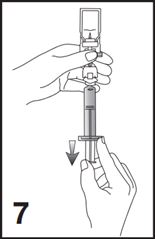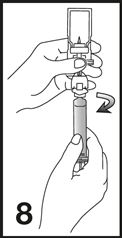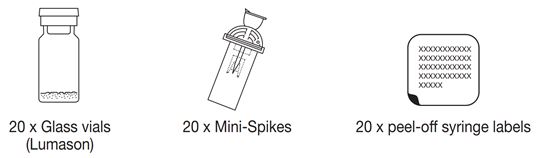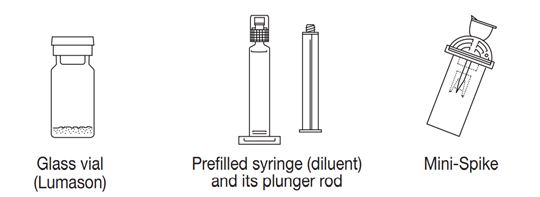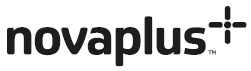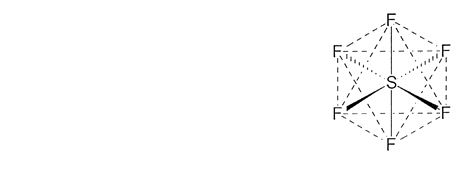 DRUG LABEL: LumaSon
NDC: 0270-7099 | Form: KIT | Route: INTRAVESICAL
Manufacturer: BRACCO DIAGNOSTICS INC
Category: prescription | Type: HUMAN PRESCRIPTION DRUG LABEL
Date: 20251216

ACTIVE INGREDIENTS: SULFUR HEXAFLUORIDE 60.7 mg/1 mg; DISTEAROYLPHOSPHATIDYLCHOLINE, DL- .19 mg/1 mg; SODIUM 1,2-DIPALMITOYL-SN-GLYCERO-3-PHOSPHO-(1'-RAC-GLYCEROL) .19 mg/1 mg
INACTIVE INGREDIENTS: POLYETHYLENE GLYCOL 4000 24.56 mg/1 mg; PALMITIC ACID .04 mg/1 mg; SODIUM CHLORIDE .9 mg/1 mL

HIGHLIGHTS OF PRESCRIBING INFORMATION

These highlights do not include all the information needed to use LUMASON® safely and effectively. See full prescribing information for LUMASON.
LUMASON (sulfur hexafluoride lipid-type A microspheres) for injectable suspension, for intravenous use or intravesical use
Initial U.S. Approval: 2014

WARNING: SERIOUS CARDIOPULMONARY REACTIONS

See full prescribing information for complete boxed warning

Serious cardiopulmonary reactions, including fatalities, have occurred uncommonly during or following the injection of ultrasound contrast agents, including sulfur hexafluoride lipid microspheres (5.1). Most serious reactions occur within 30 minutes of administration (5.1).

- Assess all patients for the presence of any condition that precludes administration (4).
- Always have resuscitation equipment and trained personnel readily available (5.1).

RECENT MAJOR CHANGES

Contraindications (4) | 4/2021
Warnings and Precautions, Hypersensitivity Reactions (5.2) | 4/2021

1 INDICATIONS AND USAGE

Lumason is an ultrasound contrast agent indicated for use

- in echocardiography to opacify the left ventricular chamber and to improve the delineation of the left ventricular endocardial border in adult and pediatric patients with suboptimal echocardiograms (1)
- in ultrasonography of the liver for characterization of focal liver lesions in adult and pediatric patients (1)
- in ultrasonography of the urinary tract for the evaluation of suspected or known vesicoureteral reflux in pediatric patients (1)

2 DOSAGE AND ADMINISTRATION

Avoid intra-arterial injection (2.1, 5.3)

See Full Prescribing Information for reconstitution instructions (2.3)

For intravenous injection:

- Echocardiography in adults: After reconstitution, administer 2 mL as an intravenous injection (2.2, 2.4)
- Echocardiography in pediatric patients: After reconstitution, administer 0.03 mL per kg as an intravenous injection up to a maximum of 2 mL per injection (2.2, 2.4)
- Ultrasonography of the liver in adults: After reconstitution, administer 2.4 mL as an intravenous injection (2.2, 2.4)
- Ultrasonography of the liver in pediatric patients: After reconstitution, administer 0.03 mL per kg as an intravenous injection, up to a maximum of 2.4 mL per injection (2.2, 2.4)
- May repeat dose one time during a single examination (2.2, 2.4)
- Follow each injection with an intravenous flush of 0.9% Sodium Chloride Injection, USP (2.2, 2.4)

For intravesical administration in pediatric patients:

- Ultrasonography of the urinary tract: After reconstitution, administer 1 mL via sterile 6 to 8F urinary catheter. Bladder should be first emptied and then partially filled with 0.9% Sodium Chloride Injection, USP before injection of Lumason (2.2, 2.4)
- After Lumason administration, continue filling the bladder with 0.9% Sodium Chloride Injection, USP until the patient has the urge to micturate or at the first sign of back pressure to the infusion (2.4)

3 DOSAGE FORMS AND STRENGTHS

- For injectable suspension: 25 mg of lipid-type A lyophilized powder with headspace fill of 60.7 mg sulfur hexafluoride in a single-patient use vial for reconstitution (3)

4 CONTRAINDICATIONS

- Hypersensitivity to sulfur hexafluoride lipid microspheres or its components, such as polyethylene glycol (PEG) (4)

5 WARNINGS AND PRECAUTIONS

- Cardiopulmonary reactions, including fatalities. Always have resuscitation equipment and trained personnel readily available (5.1)
- Hypersensitivity reactions. Serious acute hypersensitivity reactions have occurred in patients with no prior exposure to sulfur hexafluoride lipid-containing microsphere products, including patients with prior hypersensitivity reaction(s) to PEG (5.2, 6)

6 ADVERSE REACTIONS

Most common adverse reactions (incidence ≥ 0.5%) are headache and nausea (6.1).

To report SUSPECTED ADVERSE REACTIONS, contact Bracco Diagnostics Inc at 1-800-257-5181 or FDA at 1-800-FDA-1088 or www.fda.gov/medwatch

FULL PRESCRIBING INFORMATION

WARNING: SERIOUS CARDIOPULMONARY REACTIONS

Serious cardiopulmonary reactions, including fatalities, have occurred uncommonly during or following the injection of ultrasound contrast agents, including sulfur hexafluoride lipid microspheres [see Warnings and Precautions (5.1)]. Most serious reactions occur within 30 minutes of administration [see Warnings and Precautions (5.1)].

- Assess all patients for the presence of any condition that precludes administration [see Contraindications (4)].
- Always have resuscitation equipment and trained personnel readily available [see Warnings and Precautions (5.1)].

1 INDICATIONS AND USAGE

Echocardiography

Lumason is indicated for use in adult and pediatric patients with suboptimal echocardiograms to opacify the left ventricular chamber and to improve the delineation of the left ventricular endocardial border.

Ultrasonography of the Liver

Lumason is indicated for use with ultrasound of the liver in adult and pediatric patients to characterize focal liver lesions.

Ultrasonography of the Urinary Tract

Lumason is indicated for use in ultrasonography of the urinary tract in pediatric patients for the evaluation of suspected or known vesicoureteral reflux.

2 DOSAGE AND ADMINISTRATION

2.1 Important Administration Instructions

Do not administer Lumason by intra-arterial injection [see Warnings and Precautions (5.3)].

2.2 Recommended Dosage

Echocardiography

Adults

The recommended dose of Lumason after reconstitution is 2 mL administered as an intravenous bolus injection during echocardiography. During a single examination, a second injection of 2 mL may be administered to prolong contrast enhancement. Follow each Lumason injection with an intravenous flush using 5 mL of 0.9% Sodium Chloride Injection, USP.

Pediatric Patients

The recommended dose of Lumason after reconstitution in pediatric patients is 0.03 mL per kg administered as an intravenous injection during echocardiography. During a single examination, a second injection of 0.03 mL per kg may be administered, if needed. Do not exceed 2 mL per injection. Follow Lumason injection with an intravenous flush using 5 mL of 0.9% Sodium Chloride Injection, USP.

Ultrasonography of the Liver

Adults

The recommended dose of Lumason after reconstitution in adult patients is 2.4 mL administered as an intravenous injection during ultrasonography of the liver. During a single examination, a second injection of 2.4 mL may be administered, if needed. Follow Lumason injection with an intravenous flush using 5 mL of 0.9% Sodium Chloride Injection, USP.

Pediatric Patients

The recommended dose of Lumason after reconstitution in pediatric patients is 0.03 mL per kg administered as an intravenous injection during ultrasonography of the liver. During a single examination, a second injection of 0.03 mL per kg may be administered, if needed. Do not exceed 2.4 mL per injection. Follow Lumason injection with an intravenous flush of 0.9% Sodium Chloride Injection, USP.

Ultrasonography of the Urinary Tract

Pediatric Patients

The recommended dose of Lumason after reconstitution is 1 mL. The bladder may be refilled with 0.9% Sodium Chloride Injection, USP for a second cycle of voiding and imaging, without the need of a second Lumason administration.

2.3 Reconstitution Instructions

- Refer to Section 2.3.1 for instructions for using the single patient use kit with diluent provided
- Refer to Section 2.3.2 for instructions for using the 20-vial pack without diluent provided

2.3.1 Lumason Kit (single patient use kit)

Contents of Lumason Kit

- Inspect the Lumason kit and its components for signs of damage. Do not use the kit if the protective caps on the Lumason vial and prefilled syringe with 5 mL 0.9% Sodium Chloride Injection, USP are not intact or if the kit shows other signs of damage.
- Under aseptic conditions, reconstitute the Lumason vial using the following illustrated steps:

1. Connect the plunger rod to the prefilled 0.9% Sodium Chloride Injection, USP syringe barrel by screwing it clockwise into the syringe (see Figure 1).

2. Open the Mini-Spike blister and remove the syringe tip cap (see Figure 2).

3. Remove the Mini-Spike green cap and connect the syringe to the Mini-Spike by screwing it in clockwise (see Figure 3).

4. Remove the Mini-Spike spike protection and position the spike in the center of the rubber stopper of the vial. Press firmly inward until the spike is fully inserted in the stopper (see Figure 4).

5. Empty the content of the syringe into the vial by pushing on the plunger rod (see Figure 5).

6. Shake vigorously for 20 seconds, mixing all the contents in the vial (see Figure 6). A homogeneous white milky liquid indicates formation of sulfur hexafluoride lipid microspheres.

7. For preparation of doses greater than or equal to 1 mL, invert the system and slowly withdraw the intended volume of suspension into the syringe (see Figure 7). For preparation of doses less than 1 mL, withdraw 2 mL of the reconstituted suspension into the 5 mL syringe and measure the volume of Lumason to inject by using the 0.2 mL graduations between the 1 mL and 2 mL marks.

8. Unscrew the syringe from the Mini-Spike (see Figure 8). Peel and remove the diluent label to display the reconstituted product label. For intravenous administration, immediately connect the syringe to a dose administration line (20 G) and administer as directed under the Administration Instructions below. For intravesical administration, immediately connect the syringe to a sterile urinary catheter (6 French to 8 French) and administer as directed under the Administration Instructions below.

- Following reconstitution, Lumason suspension contains 1.5 to 5.6 x10^8 microspheres/mL with 45 mcg/mL of sulfur hexafluoride.
- Use immediately after reconstitution. If the suspension is not used immediately after reconstitution, resuspend the microspheres for a few seconds by hand agitation before the suspension is drawn into the syringe. Reconstituted suspension within a vial may be used for up to 3 hours from the time of its reconstitution. Maintain the vial containing the reconstituted suspension at room temperature 25°C (77°F); excursions permitted to 15° to 30°C (59° to 86°F).

2.3.2 Lumason Pack (20-vial pack)

Contents of Lumason Pack

*Please note: This presentation does not include pre-filled syringes of 0.9% Sodium Chloride Injection, USP (Diluent).

Lumason vials are to be used with the supplied Mini-Spike only.

Use only additive-free 0.9% Sodium Chloride Injection, USP for the reconstitution of Lumason.

Reconstitution

- Inspect the Lumason components for signs of damage. Do not use the Lumason vial if the protective cap on the vial is not intact or other components in the pack show signs of damage.
- Use aseptic conditions for the preparation and administration of Lumason.

1. Obtain a 5 mL syringe, with luer lock tip, and fill with 5 mL of additive-free 0.9% Sodium Chloride Injection, USP (diluent) (see Figure 1).

- Two healthcare professionals (HCPs) should verify that the solution selected for reconstitution of Lumason is additive-free 0.9% Sodium Chloride Injection, USP.
  1. Ensure that any air in the syringe is expelled.

[Note: A prefilled syringe containing additive-free 0.9% Sodium Chloride Injection, USP may be used. Ensure that any air in the syringe is expelled.]

2. Remove the Mini-Spike green cap and connect the syringe to the Mini-Spike by screwing it in clockwise (see Figure 2).

3. Remove the Mini-Spike spike protection and position the spike in the center of the rubber stopper of the vial. Press firmly inward until the spike is fully inserted in the stopper (see Figure 3).

4. Empty the entire 5 mL content of the syringe into the vial by pushing on the plunger rod (see Figure 4).

5. Shake vigorously for 20 seconds, mixing all the contents in the vial (see Figure 5). A homogeneous white milky liquid indicates formation of sulfur hexafluoride lipid microspheres.

6. To obtain required dose, invert the system and slowly withdraw the intended volume of suspension into the syringe (see Figure 6).

7. Unscrew the syringe from the Mini-Spike (see Figure 7).

8. Label the syringe using the peel-off sticker provided.

9. For intravenous administration, immediately connect the syringe to a dose administration line (20G) and administer as directed under the Administration Instructions below. For intravesical administration, immediately connect the syringe to a sterile urinary catheter (6 French to 8 French) and administer as directed under the Administration Instructions below.

- Following reconstitution, Lumason suspension contains 1.5 to 5.6 x10^8 microspheres/mL with 45 mcg/mL of sulfur hexafluoride.
- Use immediately after reconstitution. If the suspension is not used immediately after reconstitution, resuspend the microspheres for a few seconds by hand agitation before the suspension is drawn into the syringe. Reconstituted suspension within a vial may be used for up to 3 hours from the time of its reconstitution. Maintain the vial containing the reconstituted suspension at room temperature 25°C (77°F); excursions permitted to 15° to 30°C (59° to 86°F).

2.4 Administration Instructions

Inspect visually for particulate matter and discoloration prior to administration, whenever solution and container permit. The reconstituted suspension is milky-white, and does not contain visible particulate matter. Do not use the single-patient use vial for more than one patient.

Intravenous Administration

Administer Lumason as an intravenous bolus injection.

Intravesical Administration in Pediatric Patients

1. Insert a sterile 6 French to 8 French urinary catheter into the bladder under sterile conditions;
2. Empty the bladder of urine, and then fill the bladder with sterile 0.9% Sodium Chloride Injection, USP to approximately one third or half of its predicted total volume. The total bladder volume in children is calculated as [(age in years + 2) x 30] mL;
3. Administer Lumason as an intravesical bolus injection through the urinary catheter;
4. Continue filling the bladder with 0.9% Sodium Chloride Injection, USP until the patient has the urge to micturate or at the first sign of back pressure to the infusion.
5. Immediately following the first voiding, the bladder may be refilled with 0.9% Sodium Chloride Injection, USP for a second cycle of voiding and imaging, without the need of a second Lumason administration.

2.5 Imaging Guidelines

Echocardiography

After baseline non-contrast echocardiography is complete, adjust the mechanical index for the ultrasound device to 0.8 or lower. Continue ultrasound imaging following Lumason injection.

Ultrasonography of the Liver

After identification of the target focal lesion on non-contrast ultrasound examination, hold transducer still while switching scanner to low mechanical index (≤ 0.4) contrast-specific imaging. Continue ultrasound imaging following Lumason injection.

Ultrasonography of the Urinary Tract

After baseline non-contrast ultrasound examination of the kidney and bladder, switch the scanner to low mechanical index (≤0.4) contrast specific imaging. Perform continuous alternate ultrasound imaging of the bladder, ureters, and kidneys during filling and voiding of the bladder.

3 DOSAGE FORMS AND STRENGTHS

For injectable suspension: Lumason is supplied in two presentations (single patient use kit or 20-vial pack):

3-part single patient use kit comprised of:

- one Lumason clear vial containing 25 mg of lipid-type A sterile white lyophilized powder with headspace filled with 60.7 mg of sulfur hexafluoride gas
- one prefilled syringe containing 5 mL of 0.9% Sodium Chloride Injection, USP (Diluent)
- one Mini-Spike

20-vial pack comprised of:

- twenty Lumason clear vials, each containing 25 mg of lipid-type A sterile white lyophilized powder with headspace filled with 60.7 mg of sulfur hexafluoride gas
- twenty Mini-Spikes
- twenty peel-off syringe labels

Following reconstitution, Lumason is a homogeneous, milky white suspension containing 1.5 to 5.6 x 10^8 microspheres/mL with 45 mcg/mL of sulfur hexafluoride.

4 CONTRAINDICATIONS

Lumason is contraindicated in patients with known or suspected:

- Hypersensitivity to sulfur hexafluoride lipid microsphere or its components, such as polyethylene glycol (PEG) [see Warnings and Precautions (5.2) and Description (11)].

5 WARNINGS AND PRECAUTIONS

5.1 Serious Cardiopulmonary Reactions

Serious cardiopulmonary reactions, including fatalities have occurred uncommonly during or shortly following administration of ultrasound contrast agents, including Lumason. These reactions typically occurred within 30 minutes of administration. The risk for these reactions may be increased among patients with unstable cardiopulmonary conditions (acute myocardial infarction, acute coronary artery syndromes, worsening or unstable congestive heart failure, or serious ventricular arrhythmias). Always have cardiopulmonary resuscitation personnel and equipment readily available prior to Lumason administration and monitor all patients for acute reactions.

The reported reactions that may follow the administration of ultrasound contrast agents include: fatal cardiac or respiratory arrest, shock, syncope, symptomatic arrhythmias (atrial fibrillation, tachycardia, bradycardia, supraventricular tachycardia, ventricular fibrillation, and ventricular tachycardia), hypertension, hypotension, dyspnea, hypoxia, chest pain, respiratory distress, stridor, wheezing, loss of consciousness, and convulsions.

5.2 Hypersensitivity Reactions

In postmarketing use, serious hypersensitivity reactions were observed during or shortly following sulfur hexafluoride lipid-containing microsphere administration including:

Anaphylaxis, with manifestations that may include death, shock, bronchospasm, dyspnea, throat tightness, angioedema, edema (pharyngeal, palatal, mouth, peripheral, localized), swelling (face, eye, lip, tongue, upper airway), facial hypoesthesia, rash, urticaria, pruritus, flushing, and erythema.

These reactions may occur in patients with no history of prior exposure to sulfur hexafluoride lipid-containing microspheres. Lumason contains PEG. There may be increased risk of serious reactions including death in patients with prior hypersensitivity reaction(s) to PEG [see Adverse Reactions (6.2)]. Clinically assess patients for prior hypersensitivity reactions to products containing PEG, such as certain colonoscopy bowel preparations and laxatives. Always have cardiopulmonary resuscitation personnel and equipment readily available prior to Lumason administration and monitor all patients for hypersensitivity reactions.

5.3 Systemic Embolization

When administering Lumason to patients with cardiac shunt, microspheres can bypass filtering by the lung and enter the arterial circulation. Assess patients with shunts for embolic phenomena following Lumason administration. Lumason is only for intravenous and/or intravesical administration; do not administer Lumason by intra-arterial injection [see Dosage and Administration (2.1)].

5.4 Ventricular Arrhythmia Related to High Mechanical Index

High ultrasound mechanical index values may cause microsphere cavitation or rupture and lead to ventricular arrhythmias. Additionally, end-systolic triggering with high mechanical indices has been reported to cause ventricular arrhythmias.

Lumason is not recommended for use at mechanical indices greater than 0.8.

6 ADVERSE REACTIONS

The following serious adverse reactions are discussed elsewhere in the labeling:

- Cardiopulmonary reactions [see Warnings and Precautions (5.1)]
- Hypersensitivity reactions [see Warnings and Precautions (5.2)]

6.1 Clinical Trials Experience

Because clinical trials are conducted under widely varying conditions, adverse reaction rates observed in the clinical trials of a drug cannot be directly compared to rates in the clinical trials of another drug and may not reflect the rates observed in practice.

Adults

In completed clinical trials, a total of 6984 adult subjects (128 healthy volunteers and 6856 patients) received Lumason at cumulative doses ranging from 0.2 to 161 mL (mean 9.8 mL). Lumason was administered mainly as single or multiple injections; however, some subjects received infusion dosing. The majority (75%) of subjects received Lumason at cumulative doses of 10 mL or less. There were 64% men and 36% women, with an average age of 59 years (range 17 to 99 years). A total of 79% subjects were White; 4% were Black; 16% were Asian; <1% were Hispanic; and <1% were in other racial groups or race was not reported.

In the clinical trials, serious adverse reactions were observed in 2 subjects; one who experienced a hypersensitivity-type rash and presyncope and another who experienced anaphylactic shock shortly following Lumason administration.

The most commonly reported adverse reactions among patients (occurring among at least 0.2% of patients) are listed below (Table 1). Most adverse reactions were mild to moderate in intensity and resolved spontaneously.

Table 1. Adverse Reactions in Adult Patients*
n = 6856
Number (%) of Patients with Adverse Reactions | 340 (5%)
Headache | 65 (1%)
Nausea | 37 (0.5%)
Dysgeusia | 29 (0.4%)
Injection site pain | 23 (0.3%)
Feeling Hot | 18 (0.3%)
Chest discomfort | 17 (0.2%)
Chest pain | 12 (0.2%)
Dizziness | 11 (0.2%)
Injection Site Warmth | 11 (0.2%)
*occurring in at least 0.2% of patients

Pediatric Patients:

In completed clinical trials for echocardiography, a total of 12 pediatric patients received Lumason at a dose of 0.03 mL/kg. No adverse reactions were identified in pediatric patients [see Clinical Studies (14.1)].

6.2 Postmarketing Experience

In the international postmarketing clinical experience and clinical trials, serious adverse reactions have uncommonly been reported following administration of Lumason. Because these reactions are reported voluntarily from a population of uncertain size, it is not always possible to reliably estimate their frequency or establish a causal relationship to drug exposure. The serious adverse reactions include fatalities, especially in a pattern of symptoms suggestive of anaphylactoid/hypersensitivity reactions. Other serious reactions included arrhythmias and hypertensive episodes. These reactions typically occurred within 30 minutes of Lumason administration. These serious reactions may be increased among patients with pre-existing PEG hypersensitivity and/or unstable cardiopulmonary conditions (acute myocardial infarction, acute coronary artery syndromes, worsening or unstable congestive heart failure, or serious ventricular arrhythmias) [see Warnings and Precautions (5.1, 5.2)].

Hypersensitivity

Anaphylaxis, with manifestations that may include death, shock, bronchospasm, dyspnea, throat tightness, angioedema, edema (pharyngeal, palatal, mouth, peripheral, localized), swelling (face, eye, lip, tongue, upper airway), facial hypoesthesia, rash, urticaria, pruritus, flushing, and erythema.

8 USE IN SPECIFIC POPULATIONS

8.1 Pregnancy

Risk Summary

There are no data with Lumason use in pregnant women to inform any drug-associated risks. No adverse developmental outcomes were observed in animal reproduction studies with administration of sulfur hexafluoride lipid-type A microspheres in pregnant rats and rabbits during organogenesis at doses up to at least 10 and 20 times, respectively, the maximum human dose of 4.8 mL based on body surface area (see Data).

In the U.S. general population, the estimated background risk of major birth defects and miscarriage in clinically recognized pregnancies is 2-4% and 15-20%, respectively.

Data

Animal Data

Lumason was administered intravenously to rats at doses of 0.2, 1, and 5 mL/kg (approximately 0.4, 2, and 10 times the recommended maximum human dose of 4.8 mL, respectively, based on body surface area); Lumason doses were administered daily for about 30 consecutive days, from two weeks before pairing until the end of organogenesis. Lumason was administered intravenously to rabbits at doses of 0.2, 1, and 5 mL/kg (approximately 0.8, 4, and 20 times the recommended maximum human dose, respectively, based on body surface area); Lumason doses were administered daily from gestation day 6 to day 19 inclusive. No significant findings on the fetus were observed.

8.2 Lactation

Risk Summary

There are no data on the presence of Lumason in human milk, the effects on the breastfed infant, or the effects on milk production. The developmental and health benefits of breastfeeding should be considered along with the mother’s clinical need for Lumason and any potential adverse effects on the breastfed infant from Lumason or from the underlying maternal condition.

8.4 Pediatric Use

Echocardiography

Safety and effectiveness have been established for use in pediatric patients with suboptimal echocardiograms to opacify the left ventricular chamber and to improve delineation of the left endocardial border. Safety and effectiveness in pediatric patients are based on adequate and well-controlled studies in adults and are supported by a clinical study in 12 pediatric patients (mean age: 13.8 years) with extrapolation of efficacy to younger pediatric patients. No new adverse reactions were reported in the pediatric study [see Adverse Reactions (6.1) and Clinical Studies (14.1)]. Safety of intravenous use of Lumason was based on evaluation of published literature involving the use of Lumason in over 1400 pediatric patients (0 to 17 years).

Ultrasonography of the Liver

Safety and effectiveness in pediatric patients has been established for use in ultrasonography of the liver for characterization of focal liver lesions from adequate and well controlled trials in adult patients and a clinical study of 44 pediatric patients [see Clinical Studies (14)]. Safety of intravenous use of Lumason was based on evaluation of published literature involving use of Lumason in over 1400 pediatric patients. Non-fatal anaphylaxis was reported in one pediatric patient.

Ultrasonography of the Urinary Tract

Safety and effectiveness in pediatric patients has been established for use in ultrasonography of the urinary tract for the evaluation of suspected or known vesicoureteral reflux from two published studies comprising a total of 411 pediatric patients [see Clinical Studies (14)]. Safety of intravesical use of Lumason was based on evaluation of published literature involving use of Lumason in over 6000 pediatric patients. No adverse reactions were reported.

8.5 Geriatric Use

Of the total number of 6856 adult patients in clinical studies of Lumason, 39% were 65 and over, while 11% were 75 and older. No overall differences in safety or effectiveness were observed between these subjects and younger subjects, and other reported clinical experience has not identified differences in responses between the elderly or younger patients, but greater sensitivity of some older individuals cannot be ruled out.

11 DESCRIPTION

Lumason (sulfur hexafluoride lipid-type A microspheres) for injectable suspension, for intravenous or intravesical use is used to prepare the ultrasound contrast agent. Lumason is supplied in two presentations (single patient use kit or 20-vial pack):

- The single patient use kit contains the following three items:
  1. one clear glass 10 mL vial containing 25 mg of white lyophilized powder lipid-type A, 60.7 mg of sulfur hexafluoride gas and capped with a blue flip-cap
  2. one prefilled syringe containing 5 mL 0.9% Sodium Chloride Injection, USP (Diluent)
    Each prefilled syringe with 5 mL of diluent 0.9% Sodium Chloride Injection, USP is sterile, nonpyrogenic, and additive-free containing 9 mg sodium chloride per mL.
  3. one Mini-Spike
- The 20-vial pack is comprised of:
  1. twenty Lumason clear vials, each containing 25 mg of lipid-type A sterile white lyophilized powder with headspace filled with 60.7 mg of sulfur hexafluoride gas
  2. twenty Mini-Spikes
  3. twenty peel-off syringe labels

Each vial is formulated as a 25 mg sterile, pyrogen-free lyophilized powder containing 24.56 mg of polyethylene glycol 4000, 0.19 mg of distearoylphosphatidyl-choline (DSPC), 0.19 mg of dipalmitoylphosphatidylglycerol sodium (DPPG-Na) and 0.04 mg of palmitic acid. The headspace of each vial contains 6.07 mg/mL (± 2 %) sulfur hexafluoride, SF6, or 60.7 mg per vial.

Upon reconstitution with 5mL diluent, Lumason is a milky white, homogeneous suspension containing sulfur hexafluoride lipid-type A microspheres. The suspension is isotonic and has a pH of 4.5 to 7.5.

The sulfur hexafluoride lipid microspheres are composed of SF6 gas in the core surrounded by an outer shell monolayer of phospholipids consisting DSPC and DPPG-Na with palmitic acid as a stabilizer.

Sulfur hexafluoride has a molecular weight of 145.9 and the following chemical structure:

1,2-Distearoyl-sn-glycero-3-phosphocholine (DSPC), with empirical formula C44H88NO8P, has a molecular weight of 790.6 and the following chemical structure:

1,2-Dipalmitoyl-sn-glycero-3-phospho-rac-glycerol sodium (DPPG-Na), with empirical formula C38H74 NaO10P, has a molecular weight of 745 and the following chemical structure:

Each milliliter of reconstituted Lumason suspension contains 1.5 to 5.6 x10^8 microspheres, 68 mcg SF6 (12 mcL), 0.038 mg DSPC, 0.038 mg DPPG-Na, 4.91 mg polyethylene glycol 4000 and 0.008 mg palmitic acid. The sulphur hexafluoride associated with the microspheres suspension is 45 mcg/mL. Fifteen to twenty three percent of the total lipids in the suspension are associated with the microspheres.

The sulfur hexafluoride lipid microsphere characteristics are listed in Table 2:

Table 2. Microsphere Characteristics
Mean diameter range | 1.5 – 2.5 μm
Percent of microspheres ≤ 10 µm | ≥ 99%
Upper size limit | 100.0% ≤ 20 µm

12 CLINICAL PHARMACOLOGY

12.1 Mechanism of Action

Within the blood, the acoustic impedance of Lumason microspheres is lower than that of the surrounding non-aqueous tissue. Therefore, an ultrasound beam is reflected from the interface between the microspheres and the surrounding tissue. The reflected ultrasound signal provides a visual image that shows a contrast between the blood and the surrounding tissues.

For ultrasonography of the urinary tract in pediatric patients, the intravesically administered Lumason microspheres increase signal intensity of fluids within the urethra, bladder, ureters, and renal pelvis.

12.2 Pharmacodynamics

Lumason provides useful echocardiographic signal intensity for two minutes after intravenous injection. Lumason microspheres are destroyed and contrast enhancement decreases as the mechanical index increases (values of 0.8 or less are recommended).

For ultrasonography of the liver, Lumason provides dynamic patterns of differential signal intensity enhancement between focal liver lesions and liver parenchyma during the arterial, portal venous, and late phase of signal intensity enhancement of the microvasculature.

In ultrasonography of the urinary tract, Lumason facilitates the detection of reflux of fluid from the bladder into the ureters.

Pulmonary Hemodynamic Effects

The effect of Lumason on pulmonary hemodynamics was studied in a prospective, open-label study of 36 patients scheduled for right heart catheterization, including 18 with mean pulmonary arterial pressure (MPAP) > 25 mmHg and 18 with MPAP ≤ 25 mmHg. No clinically important pulmonary hemodynamic changes were observed. This study did not assess the effect of Lumason on visualization of cardiac or pulmonary structures.

12.3 Pharmacokinetics

The pharmacokinetic of the SF6 gas component of Lumason was evaluated in 12 healthy adult subjects. After intravenous bolus injections of 0.03 mL/kg and 0.3 mL/kg of Lumason, corresponding to approximately 1 and 10 times the recommended doses, concentrations of SF6 in blood peaked within 1 to 2 minutes for both doses. The terminal half-life of SF6 in blood was approximately 10 minutes for the 0.3 mL/kg dose. The area-under-the-curve of SF6 was dose-proportional over the dose range studied.

Distribution

In a study of healthy subjects, the mean values for the apparent steady-state volume of distribution of SF6 following intravenous administration, were 341 mcL and 710 mcL for Lumason doses of 0.03 mL/kg and 0.3 mL/kg, respectively. Preferential distribution to the lung is likely responsible for these values.

Elimination

Following intravenous administration, the SF6 component of Lumason is eliminated via the lungs. In a clinical study that examined SF6 elimination twenty minutes following Lumason injection, the mean cumulative recovery of SF6 in expired air was 82 ± 20% (SD) at the 0.03 mL/kg dose and 88 ± 26% (SD) at the 0.3 mL/kg dose.

SF6 undergoes first pass elimination within the pulmonary circulation; approximately 40% to 50% of the SF6 content was eliminated in the expired air during the first minute following Lumason injection.

Metabolism

SF6 undergoes little or no biotransformation; following intravenous administration, 88% of an administered dose is recovered unchanged in expired air.

Pharmacokinetics in Specific Populations

Pulmonary Impairment:

In a study of patients with pulmonary impairment, blood concentrations of SF6 peaked at 1 to 4 minutes following intravenous Lumason administration. The cumulative recovery of SF6 in expired air was 102 ± 18% (mean ± standard deviation), and the terminal half-life of SF6 in blood was similar to that measured in healthy subjects.

13 NONCLINICAL TOXICOLOGY

13.1 Carcinogenesis, Mutagenesis, Impairment of Fertility

No long-term animal studies were performed to evaluate the carcinogenic potential of Lumason. No evidence of genotoxicity was found in the following studies conducted with Lumason: 1) a bacterial mutagenesis (Ames) assay, 2) an in vitro human lymphocyte chromosome aberration assay, and 3) an in vivo mouse micronucleus assay.

No impairment of fertility was observed in rats receiving Lumason at doses up to 8 times the human dose based on body surface area.

14 CLINICAL STUDIES

14.1 Echocardiography

Adults

A total of 191 patients with suspected cardiac disease and suboptimal non-contrast echocardiography received Lumason in three multi-center controlled clinical trials (76 patients in Study A, 62 patients in Study B, and 53 patients in Study C). Among these patients, there were 127 men and 64 women. The mean age was 59 years (range 22 to 96 years). The racial and ethnic representations were 79% White, 16% Black, 4% Hispanic, < 1% Asian, and < 1% other racial or ethnic groups. The mean weight was 204 lbs (range 92 to 405 lbs). Approximately 20% of the patients had a chronic pulmonary disorder and 30% had a history of heart failure. Of the 106 patients for whom a New York Heart Association (NYHA) classification of heart failure was assigned, 49% were Class I, 33% were Class II, and 18% were Class III. Patients with NYHA Class IV heart failure were not included in these studies.

In Studies A and B, each patient received four intravenous bolus injections of Lumason (0.5, 1, 2, and 4 mL), in randomized order. In Study C, each patient received two doses of Lumason (1 mL and 2 mL) in randomized order. All three studies assessed endocardial border delineation and left ventricular opacification. For each patient in each study, echocardiography with Lumason was compared to non-contrast (baseline) echocardiography. A recording of 2D echocardiography was obtained from 30 seconds prior to each injection to at least 15 minutes after dosing or until the disappearance of the contrast effect, whichever was longer. Contrast and non-contrast echocardiographic images for each patient were evaluated by two independent reviewers, who were blinded to clinical information and the Lumason dose. Evaluation of left ventricular endocardial border consisted of segment based assessment involving six endocardial segments and using two apical views (2- and 4-chamber views).

Endocardial Border Delineation and Duration of Useful Contrast Effect

In all three studies, administration of Lumason improved left ventricular endocardial border delineation. The majority of the patients who received a 2.0 mL dose of Lumason had improvement in endocardial border delineation manifested as visualization of at least two additional endocardial border segments. Table 3 demonstrates the improvement in endocardial border delineation following Lumason administration as a reduction in percentage of patients with inadequate border delineation in at least one pair of adjacent segments (combined 2-chamber and 4-chamber view). The results are shown by reader.

Table 3. Reduction in Percentage of Patients with Inadequate Border Delineation
Reader | Study A N = 76 |  | Study B N = 62 |  | Study C N = 53
Reader | Non- contrast | Lumason | Non- contrast | Lumason | Non- contrast | Lumason
A | 60 (79%) | 22 (33%) | 31 (50%) | 12 (19%) | 12 (23%) | 10 (19%)
B | 62 (82%) | 29 (37%) | 54 (87%) | 6 (10%) | 45 (85%) | 20 (38%)

Following the first appearance of contrast within the left ventricle the mean duration of useful contrast effect ranged from 1.7 to 3.1 minutes.

Left Ventricular Opacification

In all three studies, complete left ventricular opacification was observed in 52% to 80% of the patients following administration of a 2.0 mL dose of Lumason. The studies did not sufficiently assess the effect of Lumason upon measures of left ventricular ejection fraction and wall motion.

Pediatric patients:

Twelve pediatric patients 9 to 17 years of age with suspected cardiac disease and suboptimal non-contrast echocardiography received Lumason in one prospective multicenter clinical trial. Patients received Lumason at a dose of 0.03 mL/kg (mean 1.83 mL). There were 7 female, 10 white, and 2 black patients.

For both the non-contrast and contrast-enhanced images, standard apical 4-, 2-, and 3- chamber views with harmonic imaging were acquired. Contrast and non-contrast images for each patient were evaluated by three independent reviewers, who were blinded to clinical information.

Endocardial Border Delineation

Evaluation of left ventricular endocardial border delineation consisted of segment-based assessment of the left ventricle divided into 17 endocardial segments. The delineation of each segment’s endocardial border was rated as inadequate, sufficient, or good. An exam was considered suboptimal if any of the patient’s apical views had 2 or more adjacent segments with inadequate delineation scores.

The majority of screened patients had adequate delineation of the left ventricular endocardial border without administration of contrast. The number of patients with inadequate left ventricular endocardial border delineation without contrast and after Lumason are shown for the 12 patients, by reader, in Table 4.

Table 4. Number of Pediatric Patients with Inadequate Border Delineation with and without Lumason
 | Reader A | Reader B | Reader C
Non-contrast | 12/12 | 11/11b | 12/12
Lumason | 1/11a | 0/9bb | 0/11c
a Reader A had missing segment data with contrast echocardiography for one patient;
b Reader B had missing segment data with non-contrast echocardiography for one patient;
bb Reader B had missing segment data with contrast echocardiography for three patients;
c Reader C had missing segment data with contrast echocardiography for one patient

Left Ventricular Opacification

Complete left ventricular opacification was observed in all the patients by all 3 readers following administration of Lumason.

14.2 Ultrasonography of the Liver

Adults

A total of 499 patients with at least 1 focal liver lesion requiring characterization were evaluated in two studies (259 patients in Study A, 240 patients in Study B). Among these patients, there were 259 men and 240 women. The mean age was 56 years (range 19 to 93 years). The racial and ethnic representations were 74% White, 11% Black, 9% Hispanic, 5% Asian, and 1% other racial or ethnic groups. The mean weight was 80 kg (range 44 to 173 kg).

In both studies, prior to Lumason administration, gray scale and Doppler (color or power imaging) ultrasound examinations of the target lesion were performed using commercially available ultrasound equipment and using standard techniques. Each patient received an intravenous injection of 2.4 mL of Lumason (up to 2 injections were allowed, 91% patients received 1 injection). Following Lumason administration, ultrasound examination of the target lesion was carried out using contrast-specific imaging modes operating at MI ≤ 0.4. The probe was positioned to provide optimal visualization over the target lesion and was kept in the same position for at least 180 seconds.

Truth standard included: histology/surgery, contrast CT, contrast MRI, and/or 6 month follow-up.

For each study, the interpretation of images was conducted by three independent readers who were blinded to clinical data. Lesions were characterized as malignant or benign. Separate blinded readers assessed the truth standard images.

Results of both studies demonstrated an improvement in characterization of focal liver lesions using Lumason ultrasound compared to non-contrast ultrasound images. Table 5 summarizes the efficacy results by reader.

Table 5. Diagnostic Performance of Lumason Ultrasound for Characterization of Focal Liver Lesions
Study A:
 | Sensitivity (patients with malignant lesions) N=119 |  |  | Specificity (patients with benign lesions) N=140
 | Lumason % | Non-contrast % | Difference (95% CI) | Lumason % | Non-contrast % | Difference (95% CI)
Reader 1 | 87* | 49 | 38 (30, 54) | 71 | 63 | 8 (-4, 21)
Reader 2 | 76* | 35 | 41 (29, 52) | 83* | 54 | 29 (21, 44)
Reader 3 | 92* | 16 | 76 (67, 84) | 73* | 22 | 51 (40, 61)
Study B:
 | Sensitivity (patients with malignant lesions) N=124 |  |  | Specificity (patients with benign lesions) N=116
 | Lumason % | Non-contrast % | Difference (95% CI) | Lumason % | Non-contrast % | Difference (95% CI)
Reader 4 | 65 | 53 | 12 (-1, 23) | 72* | 24 | 48 (35, 58)
Reader 5 | 61* | 41 | 20 (7, 32) | 67* | 7 | 60 (50, 70)
Reader 6 | 47 | 66 | -19 (-31, -7) | 88* | 59 | 29 (18, 40)
* Statistically significant improvement from non-contrast (p<0.05 based on McNemar’s test)

Pediatric patients

In one published study, 44 patients with an indeterminate focal liver lesion (23 males, 21 females, age range: 4-18 years, median 11.5 years) were evaluated after intravenous bolus administration of 1.2 to 2.4 mL of Lumason. The findings of Lumason ultrasound images were compared to CT, MRI or histology. Specificity was 98% (43/44 patients).

14.3 Ultrasonography of the Urinary Tract

Pediatric Patients

The efficacy of Lumason for the evaluation of pediatric patients with suspected or known vesicoureteral reflux was established in two published open-label single center studies (A and B). Patients received 1 mL of Lumason intravesically and underwent voiding urosonography (VUS). Patients were also evaluated with voiding cystourethrography (VCUG) as the reference standard. The presence or absence of urinary reflux with Lumason ultrasound was compared to the radiographic reference standard.

Study A evaluated 183 patients (94 male, 89 female; age 2 days - 44 months) with a total of 366 kidney-ureter units. The images were interpreted by one on-site reader, blinded to the reference standard. Out of 103 reference standard-positive images, Lumason VUS was positive in 89 units and falsely negative in 14 units. In 263 units with negative reference standard, the Lumason ultrasonography was negative in 226 and falsely positive in 37.

Study B evaluated 228 patients (123 male, 105 female; age 6 days -13 years) with a total of 463 kidney-ureter units (some patients had more than 2 units). The images were interpreted independently by two on-site readers, blinded to the reference standard. Out of 71 reference standard positive images, Lumason ultrasonography was positive in 57 and falsely negative in 14. In 392 units with negative reference standard, Lumason ultrasonography was negative in 302 and falsely positive in 90.

16 HOW SUPPLIED/STORAGE AND HANDLING

16.1 How Supplied

Lumason (sulfur hexafluoride lipid-type A microspheres) for injectable suspension is supplied as a single patient use kit and as a 20-vial pack as follows:

- 5 single patient use kits (NDC 0270-7099-73) with each kit containing:
  1. One Lumason vial of 25 mg lipid-type A white lyophilized powder with headspace fill of 60.7 mg of sulfur hexafluoride
  2. One prefilled syringe containing 5mL of 0.9% Sodium Chloride Injection, USP (Diluent)
  3. One Mini-Spike
  Each kit is packaged in a clear plastic container.

- 20-vial pack (NDC 0270-7097-08) containing:
  1. Twenty (20) Lumason vials of 25 mg lipid-type A white lyophilized powder with headspace fill of 60.7 mg of sulfur hexafluoride
  2. Twenty (20) Mini-Spikes
  3. Twenty (20) peel-off syringe labels

16.2 Storage and Handling

Store the kit at 25°C (77°F); excursions permitted to 15-30°C (59-86°F) [see USP Controlled Room Temperature].

17 PATIENT COUNSELING INFORMATION

Advise patients to inform their healthcare provider if they develop any symptoms of hypersensitivity after LUMASON administration including rash, wheezing, or shortness of breath.

Manufactured for:
Bracco Diagnostics Inc.
Princeton, NJ 08540
by
BRACCO Suisse SA
Plan-les-Ouates Geneve, Switzerland (Lumason lyophilized powder vial-25 mg lipid- type A/60.7 mg sulfur hexafluoride gas)

Vetter Pharma-Fertigung GmbH & Co. KG
88212 Ravensburg, Germany (0.9% Sodium Chloride Injection, USP)
or
Bracco Imaging S.p.A.
Via Ribes, 5, 10010 Colleretto Giacosa (TO), Italy (0.9% Sodium Chloride Injection, USP)

B. Braun Melsungen AG
34212 Melsungen, Germany (Mini-Spike)

This product is covered by US Patent No. 5,686,060

Novaplus is a registered trademark of Vizient, Inc.

CL1082-08

Revised: July 2024

Lumason - KIT Box Label
NDC: 0270-7099-73

PACKAGE LABEL

Lumason - Box of 5 Kits
NDC: 0270-7099-73

Lumason Vial Label
NDC: 0270-7099-73

PACKAGE LABEL

Lumason 20x Carton
NDC: 0270-7097-08

Lumason Vial Label
NDC: 0270-7097-08